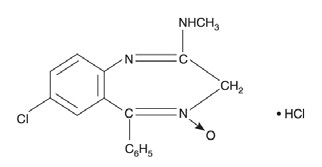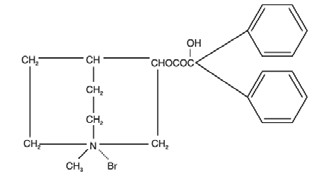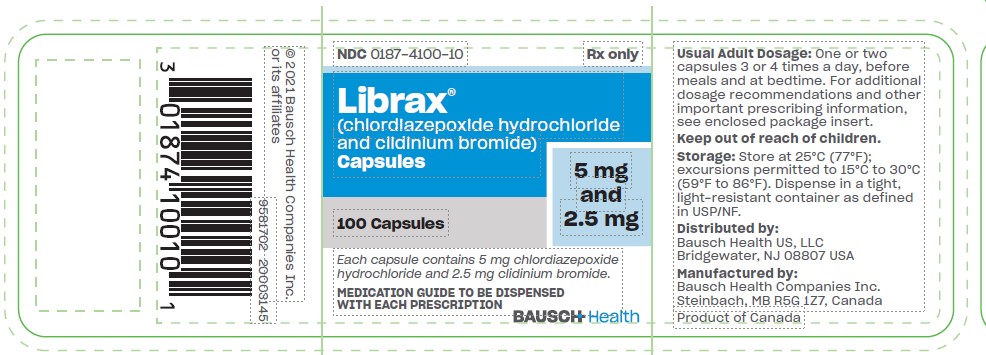 DRUG LABEL: Librax
NDC: 0187-4100 | Form: CAPSULE
Manufacturer: Bausch Health US, LLC
Category: prescription | Type: HUMAN PRESCRIPTION DRUG LABEL
Date: 20230113

ACTIVE INGREDIENTS: Chlordiazepoxide Hydrochloride 5 mg/1 1; Clidinium Bromide 2.5 mg/1 1
INACTIVE INGREDIENTS: Starch, Corn; LACTOSE, UNSPECIFIED FORM; Talc; D&C Yellow No. 10; FD&C Green No. 3; TITANIUM DIOXIDE; GELATIN, UNSPECIFIED; METHYLPARABEN; PROPYLPARABEN; POTASSIUM SORBATE

LIBRAX®
(chlordiazepoxide hydrochloride and clidinium bromide)
Capsules for oral use

WARNING: RISKS FROM CONCOMITANT USE WITH OPIOIDS; ABUSE, MISUSE, AND ADDICTION; and DEPENDENCE AND WITHDRAWAL REACTIONS

- Concomitant use of benzodiazepines and opioids may result in profound sedation, respiratory depression, coma, and death. Reserve concomitant prescribing of these drugs in patients for whom alternative treatment options are inadequate. Limit dosages and durations to the minimum required. Follow patients for signs and symptoms of respiratory depression and sedation (see WARNINGS and PRECAUTIONS and PRECAUTIONS, Drug Interactions).
- The use of benzodiazepines, including chlordiazepoxide hydrochloride, a component of Librax, exposes users to risks of abuse, misuse, and addiction, which can lead to overdose or death. Abuse and misuse of benzodiazepines commonly involve concomitant use of other medications, alcohol, and/or illicit substances, which is associated with an increased frequency of serious adverse outcomes. Before prescribing Librax and throughout treatment, assess each patient’s risk for abuse, misuse, and addiction (see WARNINGS).
- The continued use of benzodiazepines, including Librax, may lead to clinically significant physical dependence. The risks of dependence and withdrawal increase with longer treatment duration and higher daily dose. Abrupt discontinuation or rapid dosage reduction of Librax after continued use may precipitate acute withdrawal reactions, which can be life-threatening. To reduce the risk of withdrawal reactions, use a gradual taper to discontinue Librax or reduce the dosage (see WARNINGS and DOSAGE AND ADMINISTRATION).

DESCRIPTION:

Librax capsules is a fixed-combination of chlordiazepoxide hydrochloride, a benzodiazepine, and clidinium bromide, an anticholinergic.

Each Librax capsule contains the active ingredients 5 mg chlordiazepoxide hydrochloride and 2.5 mg clidinium bromide. Each capsule also contains the inactive ingredients corn starch, lactose monohydrate, talc, methylparaben, propylparaben, potassium sorbate, D&C Yellow No. 10, FD&C Green No. 3, titanium dioxide, and gelatin.

Chlordiazepoxide hydrochloride is 7-chloro-2-methylamino-5-phenyl-3H-1,4-benzodiazepine 4-oxide hydrochloride. A colorless, crystalline substance, it is soluble in water. It is unstable in solution and the powder must be protected from light. The molecular weight is 336.22. The structural formula of chlordiazepoxide hydrochloride is as follows:

Clidinium bromide is a synthetic anticholinergic agent which has been shown in experimental and clinical studies to have antispasmodic and antisecretory effects on the gastrointestinal tract.

Structurally clidinium bromide is:

ANIMAL PHARMACOLOGY AND/OR ANIMAL TOXICOLOGY:

Effects on Reproduction
Reproduction studies in rats fed chlordiazepoxide hydrochloride, 10, 20 and 80 mg/kg daily (2.4, 4.8 and 19.4 times, respectively, the maximum recommended clinical dose of 40 mg/day, based on body surface area), and bred through one or two matings showed no congenital anomalies, nor were there adverse effects on growth of the newborn. However, in another study at 100 mg/kg daily there was noted a significant decrease in the fertilization rate and a marked decrease in the viability and body weight of offspring which may be attributable to sedative activity, thus resulting in lack of interest in mating and lessened maternal nursing and care of the young. One neonate in each of the first and second matings in the rat reproduction study at the 100 mg/kg dose (24.2 times the maximum recommended human dose of 40 mg/day, based on body surface area) exhibited major skeletal defects.

Two series of reproduction experiments with clidinium bromide were carried out in rats, employing dosages of 2.5 and 10 mg/kg daily (1.2 and 4.9 times, respectively, the maximum recommended clinical dose of 20 mg/day, based on body surface area) in each experiment. In the first experiment, clidinium bromide was administered for a 9-week interval prior to mating; no untoward effect on fertilization or gestation was noted. The offspring were taken by caesarean section and did not show a significant incidence of congenital anomalies when compared to control animals. In the second experiment, adult animals were given clidinium bromide for 10 days prior to and through two mating cycles. No significant effects were observed on fertility, gestation, viability of offspring or lactation, as compared to control animals, nor was there a significant incidence of congenital anomalies in the offspring derived from these experiments.

A reproduction study was carried out in rats through two successive matings with administration of oral daily doses of 2.5 mg/kg chlordiazepoxide hydrochloride and 1.25 mg/kg clidinium bromide (0.6 times the maximum recommended clinical dose for both drugs, based on body surface area) or 25 mg/kg chlordiazepoxide hydrochloride and 12.5 mg/kg clidinium bromide (6.1 times the maximum recommended clinical dose for both drugs, based on body surface area). In the first mating, no significant differences were noted between the control or the treated groups, with the exception of a slight decrease in the number of animals surviving during lactation among those receiving the high dosage. In the second mating, similar results were obtained except for a slight decrease in the number of pregnant females and in the percentage of offspring surviving until weaning. No congenital anomalies were observed in both matings in either the control or treated groups.

INDICATIONS AND USAGE:

Librax is indicated to control emotional and somatic factors in gastrointestinal disorders. Librax may also be used as adjunctive therapy in the treatment of peptic ulcer and in the treatment of the irritable bowel syndrome (irritable colon, spastic colon, mucous colitis) and acute enterocolitis.

CONTRAINDICATIONS:

Librax is contraindicated in the presence of glaucoma (since the anticholinergic component may produce some degree of mydriasis) and in patients with prostatic hypertrophy and benign bladder neck obstruction. It is contraindicated in patients with known hypersensitivity to chlordiazepoxide hydrochloride and/or clidinium bromide.

WARNINGS:

Risks From Concomitant Use with Opioids

Concomitant use of benzodiazepines, including Librax, and opioids may result in profound sedation, respiratory depression, coma, and death. Because of these risks, reserve concomitant prescribing of these drugs - in patients for whom alternative treatment options are inadequate.

Observational studies have demonstrated that concomitant use of opioid analgesics and benzodiazepines increases the risk of drug-related mortality compared to use of opioids alone. If a decision is made to prescribe Librax concomitantly with opioids, prescribe the lowest effective dosages and minimum durations of concomitant use, and follow patients closely for signs and symptoms of respiratory depression and sedation. Advise both patients and caregivers about the risks of respiratory depression and sedation when Librax is used with opioids (see PRECAUTIONS).

Abuse, Misuse, and Addiction

The use of benzodiazepines, including chlordiazepoxide hydrochloride, a component of Librax, exposes users to the risks of abuse, misuse, and addiction, which can lead to overdose or death. Abuse and misuse of benzodiazepines often (but not always) involve the use of doses greater than the maximum recommended dosage and commonly involve concomitant use of other medications, alcohol, and/or illicit substances, which is associated with an increased frequency of serious adverse outcomes, including respiratory depression, overdose, or death (see DRUG ABUSE AND DEPENDENCE).

Before prescribing Librax and throughout treatment, assess each patient’s risk for abuse, misuse, and addiction (e.g., using a standardized screening tool). Use of Librax, particularly in patients at elevated risk, necessitates counseling about the risks and proper use of Librax along with monitoring for signs and symptoms of abuse, misuse, and addiction. Prescribe the lowest effective dosage; avoid or minimize concomitant use of CNS depressants and other substances associated with abuse, misuse, and addiction (e.g., opioid analgesics, stimulants); and advise patients on the proper disposal of unused drug. If a substance use disorder is suspected, evaluate the patient and institute (or refer them for) early treatment, as appropriate.

Dependence and Withdrawal Reactions

To reduce the risk of withdrawal reactions, use a gradual taper to discontinue Librax or reduce the dosage (a patient-specific plan should be used to taper the dosage) (see DOSAGE AND ADMINISTRATION).

Patients at an increased risk of withdrawal adverse reactions after benzodiazepine discontinuation or rapid dosage reduction include those who take higher dosages, and those who have had longer durations of use.

Acute Withdrawal Reactions

The continued use of benzodiazepines, including Librax, may lead to clinically significant physical dependence. Abrupt discontinuation or rapid dosage reduction of Librax after continued use, or administration of flumazenil (a benzodiazepine antagonist) may precipitate acute withdrawal reactions, which can be life-threatening (e.g., seizures) (see DRUG ABUSE AND DEPENDENCE).

Protracted Withdrawal Syndrome

In some cases, benzodiazepine users have developed a protracted withdrawal syndrome with withdrawal symptoms lasting weeks to more than 12 months (see DRUG ABUSE AND DEPENDENCE).

Effects on the Ability to Drive or Operate Machinery

As in the case of other preparations containing CNS-acting drugs, patients receiving Librax should be cautioned about possible combined effects with opioids, alcohol and other CNS depressants. For the same reason, they should be cautioned against hazardous occupations requiring complete mental alertness, such as operating machinery or driving a motor vehicle.

Neonatal Sedation and Withdrawal Syndrome
Use of benzodiazepines late in pregnancy can result in sedation (respiratory depression, lethargy, hypotonia) and/or withdrawal symptoms (hyperreflexia, irritability, restlessness, tremors, inconsolable crying, and feeding difficulties) in the neonate (see PRECAUTIONS, Pregnancy). Monitor neonates exposed to Librax, which contains a benzodiazepine (chlordiazepoxide hydrochloride), during pregnancy and labor for signs of sedation and monitor neonates exposed to Librax during pregnancy for signs of withdrawal; manage these neonates accordingly.

PRECAUTIONS:

CNS Adverse Reactions

In geriatric or debilitated patients, it is recommended that the dosage be limited to the smallest effective amount to preclude the development of ataxia, oversedation or confusion (not more than 2 Librax capsules per day initially, to be increased gradually as needed and tolerated). In general, the concomitant administration of Librax and other psychotropic agents is not recommended. If such combination therapy seems indicated, careful consideration should be given to the pharmacology of the agents to be employed — particularly when the known potentiating compounds such as the MAO inhibitors and phenothiazines are to be used. The usual precautions in treating patients with impaired renal or hepatic function should be observed.

Paradoxical reactions to chlordiazepoxide hydrochloride, e.g., excitement, stimulation and acute rage, have been reported in psychiatric patients and should be watched for during Librax therapy. The usual precautions are indicated when chlordiazepoxide hydrochloride is used in the treatment of anxiety states where there is any evidence of impending depression; it should be borne in mind that suicidal tendencies may be present and protective measures may be necessary.

Information for Patients

Abuse, Misuse, and Addiction

Inform patients that the use of Librax, even at recommended dosages, exposes users to risks of abuse, misuse, and addiction, which can lead to overdose and death, especially when used in combination with other medications (e.g., opioid analgesics), alcohol, and/or illicit substances. Inform patients about the signs and symptoms of benzodiazepine abuse, misuse, and addiction; to seek medical help if they develop these signs and/or symptoms; and on the proper disposal of unused drug (see WARNINGS).

Withdrawal Reactions

Inform patients that the continued use of Librax may lead to clinically significant physical dependence and that abrupt discontinuation or rapid dosage reduction of Librax may precipitate acute withdrawal reactions, which can be life-threatening. Inform patients that in some cases, patients taking benzodiazepines have developed a protracted withdrawal syndrome with withdrawal symptoms lasting weeks to more than 12 months. Instruct patients that discontinuation or dosage reduction of Librax may require a slow taper (see WARNINGSand DRUG ABUSE AND DEPENDENCE).

Concomitant Use with Opioids and Other CNS Depressants

Inform patients and caregivers that potentially fatal additive effects may occur if Librax is used with opioids or other CNS depressants, including alcohol, and not to use these concomitantly unless supervised by a health care provider (see WARNINGSand PRECAUTIONS, Drug Interactions).

Pregnancy
Advise pregnant females that use of Librax late in pregnancy can result in sedation (respiratory depression, lethargy, hypotonia) and /or withdrawal symptoms (hyperreflexia, irritability, restlessness,

tremors, inconsolable crying, and feeding difficulties) in newborns (see WARNINGS, Neonatal Sedation and Withdrawal Syndrome and PRECAUTIONS, Pregnancy). Instruct patients to inform their healthcare provider if they are pregnant.

Nursing

Instruct patients to notify their healthcare provider if they are breastfeeding or intend to breastfeed (see PRECAUTIONS, Nursing Mothers).

Drug Interactions

Opioids

The concomitant use of benzodiazepines, including chlordiazepoxide hydrochloride, a component of Librax, and opioids increases the risk of respiratory depression because of actions at different receptor sites in the CNS that control respiration. Benzodiazepines interact at GABAA sites and opioids interact primarily at mu receptors.

When benzodiazepines and opioids are combined, the potential for benzodiazepines to significantly worsen opioid-related respiratory depression exists. Limit dosage and duration of concomitant use of Librax and opioids, and follow patients closely for respiratory depression and sedation.

Oral Anticoagulants

Although clinical studies have not established a cause and effect relationship, physicians should be aware that variable effects on blood coagulation have been reported very rarely in patients receiving oral anticoagulants and chlordiazepoxide hydrochloride, a component of Librax.

Pregnancy
Risk Summary
Chlordiazepoxide Hydrochloride

Neonates born to mothers using benzodiazepines during the later stages of pregnancy have been reported to experience symptoms of sedation and/or neonatal withdrawal (see WARNINGS, Neonatal Sedation and Withdrawal Syndromeand PRECAUTIONS: Clinical Considerations). Available data from published observational studies of pregnant women exposed to benzodiazepines do not report a clear association with benzodiazepines and major birth defects (see Data).

Clidinium Bromide

Over decades of use, there is an absence of published data on orally administered clidinium bromide in pregnant women, including an absence of any reports of a drug-associated risk of major birth defects, miscarriage, or other adverse maternal or fetal outcomes. The background risk of major birth defects and miscarriage for the indicated population is unknown. All pregnancies have a background risk of birth defect, loss, or other adverse outcomes. In the U.S. general population, the estimated risk of major birth defects and miscarriage in clinically recognized pregnancies is 2% to 4% and 15% to 20%, respectively.

Clinical Considerations

Fetal/Neonatal Adverse Reactions

Benzodiazepines cross the placenta and may produce respiratory depression, hypotonia and sedation in neonates. Monitor neonates exposed to Librax, which contains a benzodiazepine (chlordiazepoxide hydrochloride), during pregnancy or labor for signs of sedation, respiratory depression, hypotonia, and feeding problems. Monitor neonates exposed to Librax during pregnancy for signs of withdrawal. Manage these neonates accordingly (see WARNINGS, Neonatal Sedation and Withdrawal Syndrome).

Data

Human Data

Published data from observational studies on the use of benzodiazepines during pregnancy do not report a clear association with benzodiazepines and major birth defects. Although early studies reported an increased risk of congenital malformations with diazepam and chlordiazepoxide, there was no consistent pattern noted. In addition, the majority of more recent case-control and cohort studies of benzodiazepine use during pregnancy, which were adjusted for confounding exposures to alcohol. Tobacco and other medications, have not confirmed these findings.

Animal Data

Oral daily doses of 2.5 mg/kg chlordiazepoxide hydrochloride with 1.25 mg/kg clidinium bromide or 25 mg/kg chlordiazepoxide hydrochloride with 12.5 mg/kg clidinium bromide (0.6 and 6.1 times, respectively, the maximum recommended clinical dose for both drugs, based on body surface area) were administered to rats in a reproduction study through two successive matings. In the first mating, no significant differences were noted between the control or the treated groups, with the exception of a slight decrease in the number of animals surviving during lactation among those receiving the highest dosage. In the second mating, similar results were obtained except for a slight decrease in the number of pregnant females and in the percentage of offspring surviving until weaning. No congenital anomalies were observed in both matings in either the control or treated groups.

Nursing Mothers

Chlordiazepoxide Hydrochloride

There are no data on the presence of chlordiazepoxide in either human or animal milk, the effects on the breastfed infant, or the effects on milk production. However, there are reports of sedation, poor feeding and poor weight gain in infants exposed to other benzodiazepines through breast milk. Reproduction studies in rats fed chlordiazepoxide hydrochloride, 10, 20 and 80 mg/kg daily (2.4, 4.8 and 19.4 times respectively, the maximum recommended clinical dose of 40 mg/day, based on body surface area), and bred through one or two matings showed no adverse effects on lactation of the dams.

Clidinium Bromide

There are no data on the presence of clidinium in either human or animal milk, the effects on the breastfed infant, or the effects on milk production. As with other anticholinergic drugs, clidinium may cause suppression of lactation.

The developmental and health benefits of breastfeeding should be considered along with the mother’s clinical need for Librax and any potential adverse effects on the breastfed infant from Librax. Infants exposed to Librax through breast milk should be monitored for sedation, poor feeding and poor weight gain.

Pediatric Use

Safety and effectiveness in pediatric patients have not been established.

Geriatric Use

Geriatric subjects may be particularly prone to experiencing drowsiness, ataxia and confusion while receiving Librax. These effects can usually be avoided with proper dosage adjustment, although they have occasionally been observed even at the lower dosage ranges. Dosing in geriatric subjects should be initiated cautiously (no more than 2 capsules per day) and increased gradually if needed and tolerated (see DOSAGE AND ADMINISTRATION). Librax is contraindicated in the presence of glaucoma, prostatic hypertrophy and benign bladder neck obstruction (see CONTRAINDICATIONS).

ADVERSE REACTIONS:

No side effects or manifestations not seen with either compound alone have been reported with the administration of Librax. However, since Librax contains chlordiazepoxide hydrochloride and clidinium bromide, the possibility of untoward effects which may be seen with either of these two compounds cannot be excluded.

When chlordiazepoxide hydrochloride has been used alone the necessity of discontinuing therapy because of undesirable effects has been rare. Drowsiness, ataxia and confusion have been reported in some patients — particularly the elderly and debilitated. While these effects can be avoided in almost all instances by proper dosage adjustment, they have occasionally been observed at the lower dosage ranges. In a few instances syncope has been reported.

Other adverse reactions reported during therapy with chlordiazepoxide hydrochloride include isolated instances of skin eruptions, edema, minor menstrual irregularities, nausea and constipation, extrapyramidal symptoms, as well as increased and decreased libido. Such side effects have been infrequent and are generally controlled with reduction of dosage. Changes in EEG patterns (low-voltage fast activity) have been observed in patients during and after chlordiazepoxide hydrochloride treatment.

Blood dyscrasias, including agranulocytosis, jaundice and hepatic dysfunction have occasionally been reported during therapy with chlordiazepoxide hydrochloride. When chlordiazepoxide hydrochloride treatment is protracted, periodic blood counts and liver function tests are advisable.

Adverse effects reported with use of Librax are those typical of anticholinergic agents, i.e., dryness of the mouth, blurring of vision, urinary hesitancy and constipation. Constipation has occurred most often when Librax therapy has been combined with other spasmolytic agents and/or a low residue diet.

To report SUSPECTED ADVERSE REACTIONS, contact Bausch Health US, LLC at 1-800-321-4576 or FDA at 1-800-FDA-1088 or www.fda.gov/medwatch.

DRUG ABUSE AND DEPENDENCE:

Controlled Substance

Librax contains chlordiazepoxide hydrochloride, a Schedule IV controlled substance and clidinium bromide, which is not a controlled substance. Librax is exempted from Schedule IV and is not controlled under the Controlled Substances Act.

Abuse

Chlordiazepoxide hydrochloride, a component of Librax, is a CNS depressant with a potential for abuse and addiction. Abuse is the intentional, non-therapeutic use of a drug, even once, for its desirable psychological or physiological effects. Misuse is the intentional use, for therapeutic purposes, of a drug by an individual in a way other than prescribed by a health care provider or for whom it was not prescribed. Drug addiction is a cluster of behavioral, cognitive, and physiological phenomena that may include a strong desire to take the drug, difficulties in controlling drug use (e.g., continuing drug use despite harmful consequences, giving a higher priority to drug use than other activities and obligations), and possible tolerance or physical dependence. Even taking benzodiazepines as prescribed may put patients at risk for abuse and misuse of their medication. Abuse and misuse of benzodiazepines may lead to addiction.

Abuse and misuse of benzodiazepines often (but not always) involve the use of doses greater than the maximum recommended dosage and commonly involve concomitant use of other medications, alcohol, and/or illicit substances, which is associated with an increased frequency of serious adverse outcomes, including respiratory depression, overdose, or death. Benzodiazepines are often sought by individuals who abuse drugs and other substances, and by individuals with addictive disorders (see WARNINGS).

The following adverse reactions have occurred with benzodiazepine abuse and/or misuse: abdominal pain, amnesia, anorexia, anxiety, aggression, ataxia, blurred vision, confusion, depression, disinhibition, disorientation, dizziness, euphoria, impaired concentration and memory, indigestion, irritability, muscle pain, slurred speech, tremors, and vertigo. The following severe adverse reactions have occurred with benzodiazepine abuse and/or misuse: delirium, paranoia, suicidal ideation and behavior, seizures, coma, breathing difficulty, and death. Death is more often associated with polysubstance use (especially benzodiazepines with other CNS depressants such as opioids and alcohol).

Dependence

Physical Dependence

Librax may produce physical dependence from continued therapy. Physical dependence is a state that develops as a result of physiological adaptation in response to repeated drug use, manifested by withdrawal signs and symptoms after abrupt discontinuation or a significant dose reduction of a drug. Abrupt discontinuation or rapid dosage reduction of benzodiazepines or administration of flumazenil, a benzodiazepine antagonist, may precipitate acute withdrawal reactions, including seizures, which can be life-threatening. Patients at an increased risk of withdrawal adverse reactions after benzodiazepine discontinuation or rapid dosage reduction include those who take higher dosages (i.e., higher and/or more frequent doses) and those who have had longer durations of use (see WARNINGS).

To reduce the risk of withdrawal reactions, use a gradual taper to discontinue Librax or reduce the dosage (see WARNINGSand DOSAGE AND ADMINISTRATION).

Acute Withdrawal Signs and Symptoms

Acute withdrawal signs and symptoms associated with benzodiazepines have included abnormal involuntary movements, anxiety, blurred vision, depersonalization, depression, derealization, dizziness, fatigue, gastrointestinal adverse reactions (e.g., nausea, vomiting, diarrhea, weight loss, decreased appetite), headache, hyperacusis, hypertension, irritability, insomnia, memory impairment, muscle pain and stiffness, panic attacks, photophobia, restlessness, tachycardia, and tremor. More severe acute withdrawal signs and symptoms, including life-threatening reactions, have included catatonia, convulsions, delirium tremens, depression, hallucinations, mania, psychosis, seizures and suicidality.

Protracted Withdrawal Syndrome
Protracted withdrawal syndrome associated with benzodiazepines is characterized by anxiety, cognitive impairment, depression, insomnia, formication, motor symptoms (e.g., weakness, tremor, muscle twitches), paresthesia, and tinnitus that persists beyond 4 to 6 weeks after initial benzodiazepine withdrawal. Protracted withdrawal symptoms may last weeks to more than 12 months. As a result, there may be difficulty in differentiating withdrawal symptoms from potential re-emergence or continuation of symptoms for which the benzodiazepine was being used.

Tolerance

Tolerance to Librax may develop from continued therapy. Tolerance is a physiological state characterized by a reduced response to a drug after repeated administration (i.e., a higher dose of a drug is required to produce the same effect that was once obtained at a lower dose). Tolerance to the therapeutic effects of Librax may develop; however, little tolerance develops to the amnestic reactions and other cognitive impairments caused by benzodiazepines.

OVERDOSAGE

Overdosage of Librax, which contains a benzodiazepine (chlordiazepoxide hydrochloride) and an anticholinergic (clidinium bromide) may manifest signs and symptoms related to either of its components, although some effects such as altered levels of consciousness may be synergistic. Overdosage of benzodiazepines, such as chlordiazepoxide hydrochloride, is characterized by central nervous system depression ranging from drowsiness to coma. In mild to moderate cases, symptoms can include drowsiness, confusion, dysarthria, lethargy, hypnotic state, diminished reflexes, ataxia, and hypotonia. Rarely, paradoxical or disinhibitory reactions (including agitation, irritability, impulsivity, violent behavior, confusion, restlessness, excitement, and talkativeness) may occur. In severe overdosage cases, patients may develop respiratory depression and coma.

Signs and symptoms of anticholinergic overdosage are related to excessive anti-muscarinic anticholinergic activity. Peripheral signs and symptoms may include dry mucous membranes and skin, flushing, tachycardia, hypertension, ileus, urinary retention, and mydriasis. Garbled speech is often pathognomonic. Central signs and symptoms may include agitation and delirium, seizures, and hyperthermia. Benzodiazepines are considered a first-line treatment for anticholinergic toxicity acting to treat mild to moderate agitation and prevent seizures.

Overdosage of benzodiazepines in combination with other CNS depressants (including alcohol and opioids) may be fatal (see WARNINGS, Dependence and Withdrawal Reactions). Markedly abnormal (lowered or elevated) blood pressure, heart rate, or respiratory rate raise the concern that additional drugs and/or alcohol are involved in the overdosage. Anticholinergic drugs usually increase heart rate and blood pressure. In managing benzodiazepine overdosage, employ general supportive measures, including intravenous fluids, and airway management.

Flumazenil, a specific benzodiazepine receptor antagonist is indicated for the complete or partial reversal of the sedative effects of benzodiazepines in the management of benzodiazepine overdosage. Use of flumazenil may increase the risk of seizures in mixed overdosage with drugs that may precipitate seizures, including anticholinergic medications. Benzodiazepines are used to treat agitated delirium from anticholinergic toxicity. Therefore flumazenil administration may worsen the anticholinergic delirium and should generally be avoided.

Anticholinesterase inhibitors may reverse severe agitated delirium that is not controlled by benzodiazepines. They may also improve the airway and breathing in CNS depressed patients. Caution is warranted especially in mixed drug overdoses.

Consider contacting a poison center (1-800-222-1222) or a medical toxicologist for overdosage management recommendations.

DOSAGE AND ADMINISTRATION:

Recommended Dosage

Because of the varied individual responses to tranquilizers and anticholinergics, the optimum dosage of Librax varies with the diagnosis and response of the individual patient. The dosage, therefore, should be individualized for maximum beneficial effects. The usual maintenance dose is 1 or 2 capsules, 3 or 4 times a day administered before meals and at bedtime.

Recommended Geriatric Dosage

Dosage should be limited to the smallest effective amount to preclude the development of ataxia, oversedation or confusion. The initial dose should not exceed 2 Librax capsules per day, to be increased gradually as needed and tolerated. Elderly patients have an increased risk of dose-related adverse reactions (see PRECAUTIONS).

Discontinuation or Dosage Reduction of Librax

To reduce the risk of withdrawal reactions, use a gradual taper to discontinue Librax or reduce the dosage. If a patient develops withdrawal reactions, consider pausing the taper or increasing the dosage to the previous tapered dosage level. Subsequently decrease the dosage more slowly (see WARNINGSand DRUG ABUSE AND DEPENDENCE).

HOW SUPPLIED:

Librax is available in light green opaque capsules, each containing 5 mg chlordiazepoxide hydrochloride and 2.5 mg clidinium bromide in bottles of 100 (NDC 0187-4100-10), with “LIBRAX® ICN” imprinted on the body of the capsule.

Store at 25°C (77°F); excursions permitted to 15°C to 30°C (59°F to 86°F).

Keep out of reach of children.

Dispense in tight, light-resistant container as defined in USP/NF.

Distributed by:
Bausch Health US, LLC
Bridgewater, NJ 08807 USA

Manufactured by:
Bausch Health Companies Inc.
Steinbach, MB R5G 1Z7, Canada

LIBRAX is a trademark of Bausch Health Companies Inc. or its affiliates.

© 2023 Bausch Health Companies Inc. or its affiliates

Revised: 01/2023

9548904
2005280

Medication Guide

LIBRAX® (lee braks)

(chlordiazepoxide hydrochloride and clidinium bromide) Capsules

for oral use

What is the most important information I should know about Librax?

- Librax contains a benzodiazepine medicine. Taking Librax with opioid medicines, alcohol, or other central nervous system (CNS) depressants (including street drugs) can cause severe drowsiness, breathing problems (respiratory depression), coma, and death. Get emergency help right away if any of the following happens:
  - shallow or slowed breathing
  - breathing stops (which may lead to the heart stopping)
  - excessive sleepiness (sedation)
Do not drive or operate heavy machinery until you know how taking Librax with opioids affects you.
- Risk of abuse, misuse, and addiction. There is a risk of abuse, misuse, and addiction with benzodiazepines, including Librax, which can lead to overdose or death.
  - Serious side effects including coma and death have happened in people who have abused or misused benzodiazepines, including Librax. These serious side effects may also include delirium, paranoia, suicidal thoughts or actions, seizures, and difficulty breathing. Call your healthcare provider or go to the nearest hospital emergency room right away if you get any of these serious side effects.
  - You can develop an addiction even if you take Librax as prescribed by your healthcare provider.
  - Take Librax exactly as your healthcare provider prescribed.
  - Do not share your Librax with other people.
  - Keep Librax in a safe place and away from children.
- Physical dependence and withdrawal reactions. Librax can cause physical dependence and withdrawal reactions.
  - Do not suddenly stop using Librax. Stopping Librax suddenly can cause serious and life-threatening side effects, including unusual movements, responses, or expressions, seizures, sudden and severe mental or nervous system changes, depression, seeing or hearing things that others do not see or hear, an extreme increase in activity or talking, losing touch with reality, and suicidal thoughts or actions. Call your healthcare provider or go to the nearest hospital emergency room right away if you get any of these symptoms.
  - Some people who suddenly stop benzodiazepines have symptoms that can last for several weeks to more than 12 months, including anxiety, trouble remembering, learning, or concentrating, depression, problems sleeping, feeling like insects are crawling under your skin, weakness, shaking, muscle twitches, burning or prickling feeling in your hands, arms, legs or feet, and ringing in your ears.
  - Physical dependence is not the same as drug addiction. Your healthcare provider can tell you more about the differences between physical dependence and drug addiction.
  - Do not take more Librax than prescribed or take Librax for longer than prescribed.

What is Librax?

- Librax is a prescription medicine that is used with other therapies for the treatment of:
  - stomach (peptic) ulcers
  - irritable bowel syndrome (IBS)
  - inflammation of the colon called acute enterocolitis
- Librax contains the medicines chlordiazepoxide hydrochloride and clidinium bromide.
- Librax contains chlordiazepoxide hydrochloride that can be abused or lead to dependence. Keep Librax in a safe place to prevent misuse and abuse. Selling or giving away Librax may harm others. Tell your healthcare provider if you have abused or been dependent on alcohol, prescription medicines or street drugs.
- It is not known if Librax is safe and effective in children.

Do not take Librax if you:

- have glaucoma
- have an enlarged prostate
- have a blockage of your bladder that causes problems with urination
- are allergic to chlordiazepoxide hydrochloride or clidinium bromide

Before you take Librax, tell your healthcare provider about all of your medical conditions, including if you:

- have eye problems
- have problems urinating or emptying your bladder
- have coordination problems
- have kidney or liver problems
- have a history of depression, mental illness, or suicidal thoughts
- have a history of drug or alcohol abuse or addiction
- have bleeding problems
- are pregnant or plan to become pregnant. Librax may harm your unborn baby.
  - Taking Librax late in pregnancy may cause your baby to have symptoms of sedation (breathing problems, sluggishness, low muscle tone), and/or withdrawal symptoms (jitteriness, irritability, restlessness, shaking, excessive crying, feeding problems).
  - Tell your healthcare provider right away if you become pregnant or think you are pregnant during treatment with Librax.
- are breastfeeding or plan to breastfeed. Librax may pass through your breast milk and may cause sedation, poor feeding or poor weight gain in your baby. Talk to your healthcare provider about the best way to feed your baby if you take Librax. Librax may decrease the amount of breast milk your body makes.

Tell your healthcare provider about all the medicines you take, including prescription and over-the-counter medicines, vitamins, and herbal supplements.

Taking Librax with certain other medicines can cause side effects or affect how well Librax or the other medicines work. Do not start or stop other medicines without talking to your healthcare provider.

Especially tell your healthcare provider if you:

- take a monoamine oxidase inhibitor (MAOI) medicine or an anti-psychotic medicine called phenothiazine.

How should I take Librax?

- Take Librax exactly as your healthcare provider tells you to take it.
- Your healthcare provider may change your dose of Librax if needed. Do not change your dose of Librax or suddenly stop taking Librax without talking with your healthcare provider.
- If you take too much Librax, call your healthcare provider or go to the nearest hospital emergency room right away.

What are the possible side effects of Librax?

Librax may cause serious side effects, including: See “What is the most important information I should know about Librax?”

- Librax can make you sleepy or dizzy and can slow your thinking and motor skills.
  - Do not drive, operate heavy machinery, or do other dangerous activities until you know how Librax affects you.
  - Do not drink alcohol or take other drugs that may make you sleepy or dizzy while taking Librax without first talking to your healthcare provider. When taken with alcohol or drugs that cause sleepiness or dizziness, Librax may make your sleepiness or dizziness much worse.

The most common side effects of Librax include:

- dry mouth
- blurred vision

- nausea
- constipation

- skin problems
- swelling

- irregular menstrual (periods) cycles
- increase and decreased desire for sex (libido)
- problems starting to urinate
- drowsiness, coordination problems, and confusion may happen, especially in people who are elderly or weak

These are not all the possible side effects of Librax.

Call your doctor for medical advice about side effects. You may report side effects to FDA at 1-800-FDA-1088.

How should I store Librax?

- Store Librax at room temperature 77°F (25°C).
- Keep Librax and all medicines out of the reach of children.

General information about the safe and effective use of Librax.

Medicines are sometimes prescribed for purposes other than those listed in a Medication Guide. Do not take Librax for a condition for which it was not prescribed. Do not give Librax to other people, even if they have the same symptoms that you have. It may harm them. You can ask your pharmacist or healthcare provider for information about Librax that is written for health professionals.

What are the ingredients in Librax?

Active ingredients: chlordiazepoxide hydrochloride and clidinium bromide

Inactive ingredients: corn starch, lactose monohydrate, and talc. Gelatin capsule shells may contain methylparaben, propylparaben, and potassium sorbate, with the following dye systems: D&C Yellow No. 10 and FD&C Green No. 3, titanium dioxide, and gelatin.

Distributed by:
Bausch Health US, LLC
Bridgewater, NJ 08807 USA

Manufactured by:
Bausch Health Companies Inc.
Steinbach, MB R5G 1Z7, Canada

For more information, go to bauschhealth.com or contact Bausch Health US, LLC at 1-800-321-4576.

LIBRAX is a trademark of Bausch Health Companies Inc. or its affiliates.

© 2023 Bausch Health Companies Inc. or its affiliates

This Medication Guide has been approved by the U.S. Food and Drug Administration.
  9548904
  2005280
Revised: 01/2023

PACKAGE/LABEL PRINCIPAL DISPLAY PANEL - Label

NDC 0187-4100-10

Rx only

Librax®

(chlordiazepoxide hydrochloride
and clindinium bromide)
Capsules

5 mg
and
2.5 mg

100 Capsules

Each capsule contains 5 mg chlordiazepoxide hydrochloride
and 2.5 mg clindinium bromide.

MEDICATION GUIDE TO BE DISPENSED
WITH EACH PRESCRIPTION

BAUSCH Health

9581702
20003145